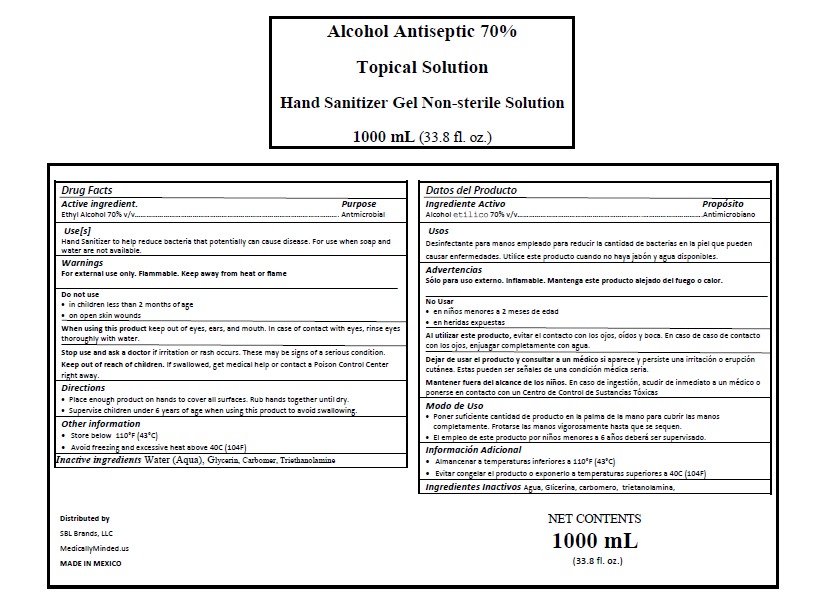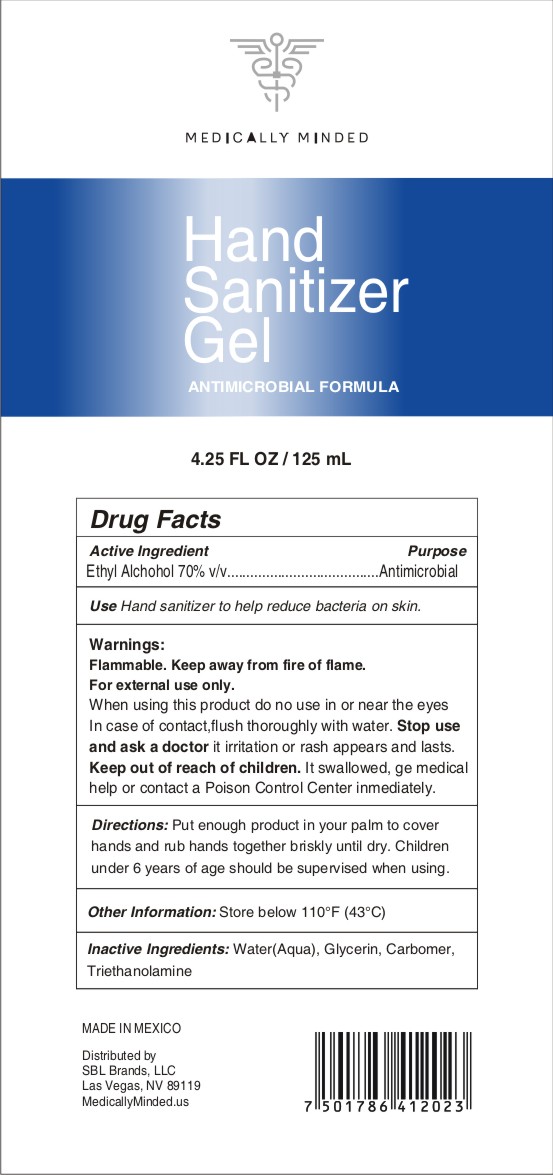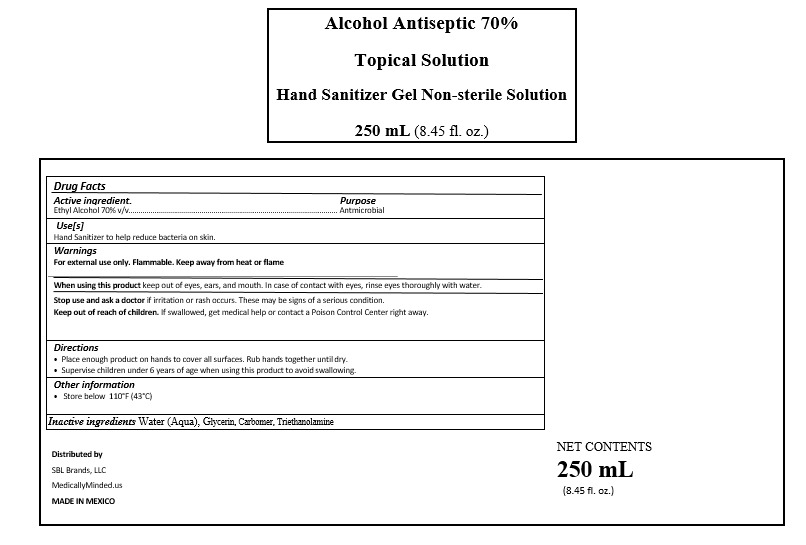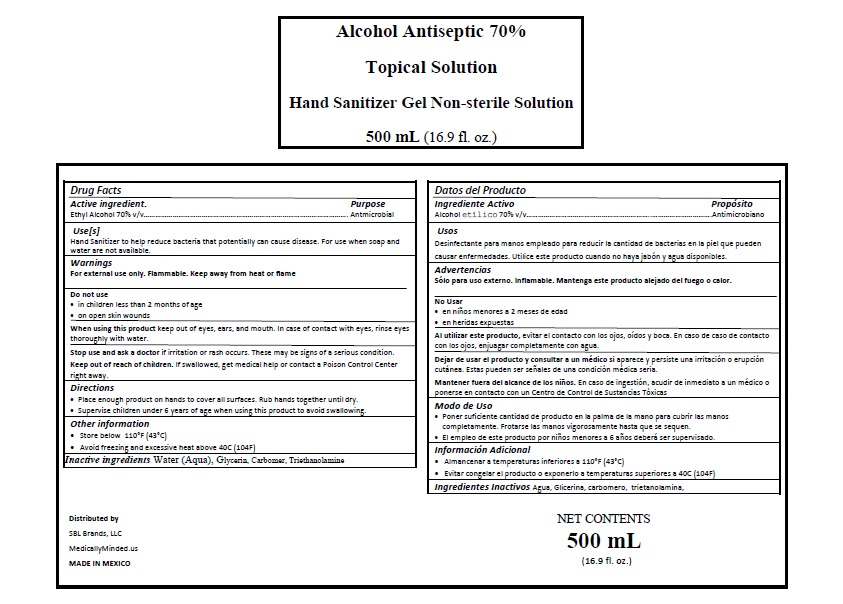 DRUG LABEL: HAND SANITIZER
NDC: 78525-2000 | Form: GEL
Manufacturer: REALITY PHARMA, S.A. DE C.V.
Category: otc | Type: HUMAN OTC DRUG LABEL
Date: 20200602

ACTIVE INGREDIENTS: ALCOHOL 0.7 mL/1 mL
INACTIVE INGREDIENTS: TRIETHANOLAMINE CAPROYL GLUTAMATE 0.002 mL/1 mL; CARBOMER 940 0.002 mL/1 mL; WATER 0.2585 mL/1 mL; GLYCERIN 0.0375 mL/1 mL

HAND SANITIZER GEL

DOSAGE

Place enough product on hands to cover all surfaces. Rub hands together until dry.

INACTIVE INGREDIENTS

Inactive ingredients Water (Aqua), Glycerin, Carbomer, Triethanolamine

DIRECTIONS

Place enough product on hands to cover all surfaces. Rub hands together until dry.

Keep out of reach of children. If swallowed, get medical help or contact a Poison Control Center right away.

PURPOSE

PURPOSE ANTIMICROBIAL

WARNINGS

For external use only. Flammable. Keep away from heat or flame

ACTIVE INGREDIENT

Active ingredient. Ethyl Alcohol 70% v/v

STOP USE ASK A DOCTOR

Stop use and ask a doctor if irritation or rash occurs. These may be signs of a serious condition.